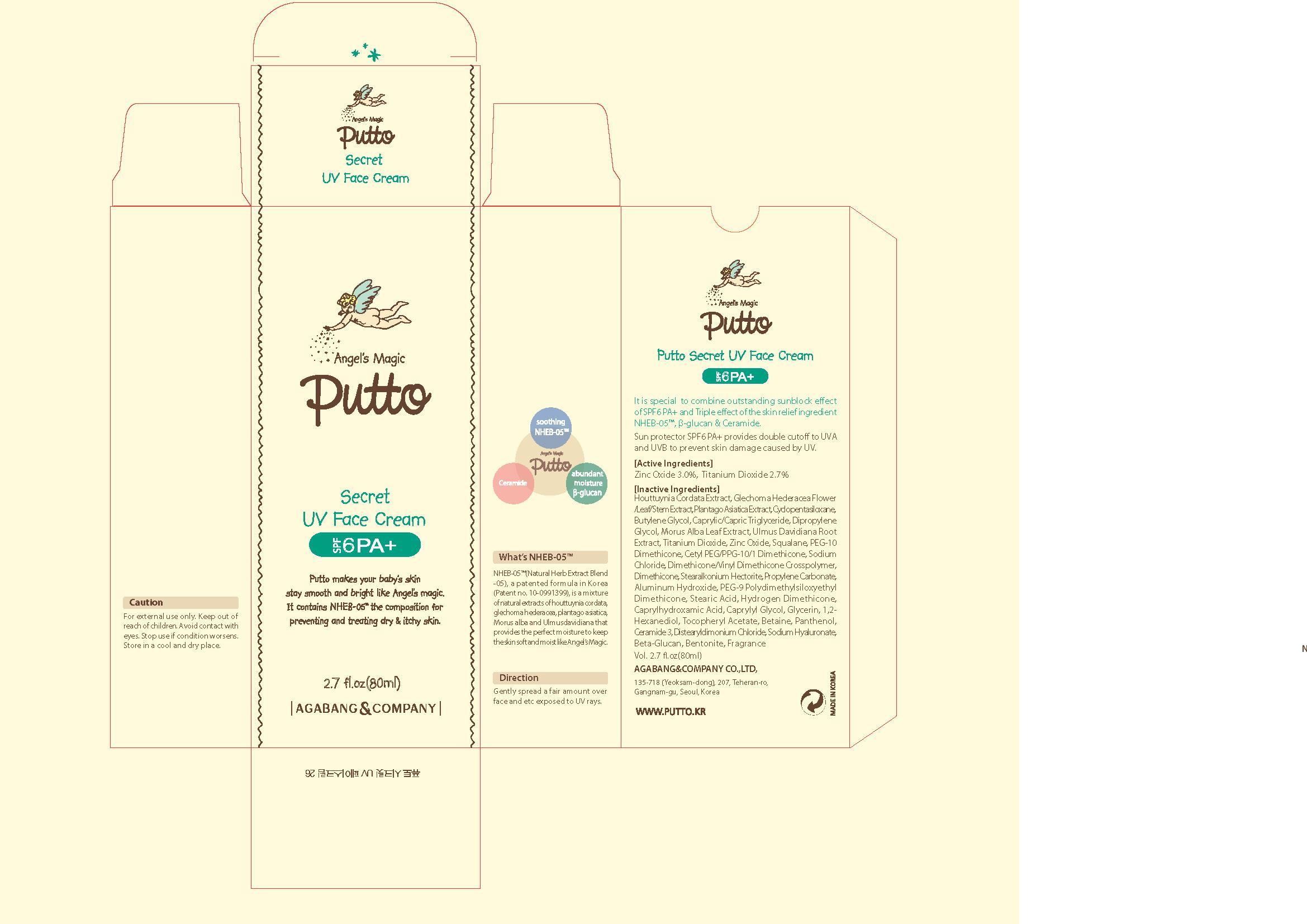 DRUG LABEL: Putto Secret UV Face
NDC: 75885-040 | Form: CREAM
Manufacturer: AGABANG & COMPANY 
Category: otc | Type: HUMAN OTC DRUG LABEL
Date: 20130903

ACTIVE INGREDIENTS: TITANIUM DIOXIDE 2.96 mg/100 mL
INACTIVE INGREDIENTS: CYCLOMETHICONE 5; GLECHOMA HEDERACEA FLOWERING TOP; HOUTTUYNIA CORDATA FLOWERING TOP; PLANTAGO ASIATICA; SQUALENE; SODIUM CHLORIDE; DIMETHICONE; DIPROPYLENE GLYCOL; GLYCERIN; MORUS ALBA LEAF; ULMUS DAVIDIANA ROOT; ALGELDRATE; PANTHENOL

Drug Facts

ACTIVE INGREDIENT

titanium dioxide

INACTIVE INGREDIENT

houttuynia cordata ext, glechoma hederacea flower/leaf/stem ext, plantago asiatica ext, cyclopentasiloxane, butylene glycol, crprylic/capric triglyceride, dipropylene glycol, morus alba leaf ext, ulmus davidiana root ext, zinc oxide, squalane, peg-10 dimethicone, cetyl peg/ppg-10/1 dimethicone, sodium chloride, dimethicone/vinyl dimethicone crosspolymer, dimethicone, stearalkonium hectorite, propylene carbonate, aluminum hydroxide, peg-9 polydimethylsiloxyethyl dimethicone, stearic acid,hydrogen dimethicone, caprylhydroxamic acid, caprylyl glycol, glycerin, 1,2-hexanediol, tocopheryl acetate betaine, panthenol, ceramide 3, distearyldimonium chloride, sodium hyaluronate, beta-glucan, bentonite, fragrance

PURPOSE

sun screen

keep out of reach of the children

INDICATIONS AND USAGE

gently spread a fair amount over face, neck, arm and etc esposed to UV rays

WARNINGS

do not apply to sensitive skin
store in a cool, dry place

DOSAGE AND ADMINISTRATION

for external use only